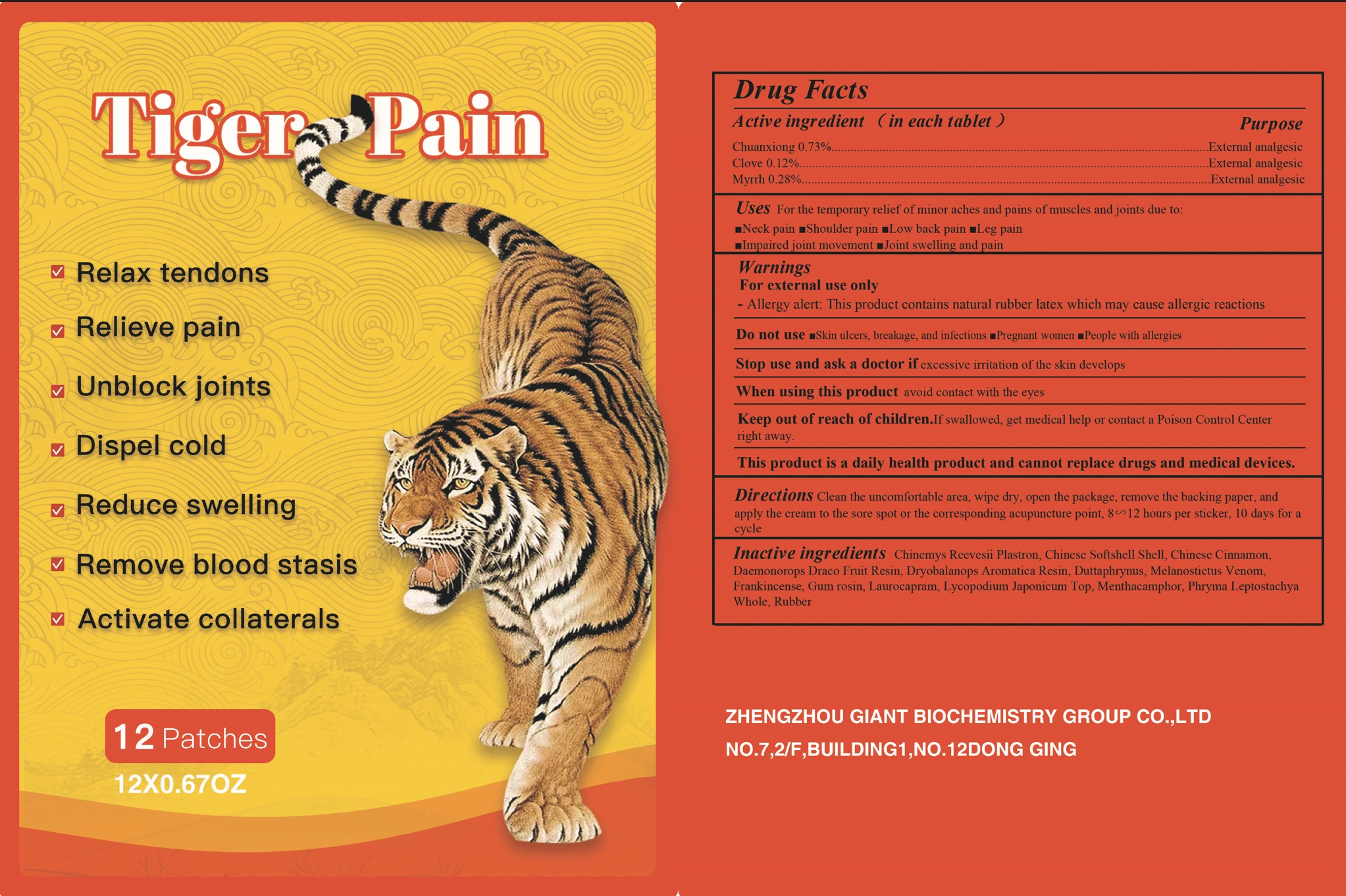 DRUG LABEL: Tiger Pain
NDC: 52784-021 | Form: PATCH
Manufacturer: ZHENGZHOU GIANT BIOCHEMISTRY GROUP CO.,LTD
Category: otc | Type: HUMAN OTC DRUG LABEL
Date: 20231218

ACTIVE INGREDIENTS: LIGUSTICUM SINENSE SUBSP. CHUANXIONG ROOT 0.73 g/100 g; CLOVE 0.12 g/100 g; MYRRH 0.28 g/100 g
INACTIVE INGREDIENTS: PELODISCUS SINENSIS SHELL; LYCOPODIUM JAPONICUM TOP; PHRYMA LEPTOSTACHYA WHOLE; MENTHOL; DRYOBALANOPS AROMATICA RESIN; NATURAL LATEX RUBBER; DUTTAPHRYNUS MELANOSTICTUS VENOM; DAEMONOROPS DRACO RESIN; CHINEMYS REEVESII PLASTRON; CHINESE CINNAMON; FRANKINCENSE; LAUROCAPRAM; ROSIN

52784-021

Active ingredient

Chuanxiong 0.73%

Clove 0.12%

Myrrh 0.28%

Purpose

External analgesic

Use

For the temporary relief of minor aches and pains of muscles and joints due to:

■Neck pain ■Shoulder pain ■Low back pain ■Leg pain ■Impaired joint movement ■Joint swelling and pain

Warnings

For external use only

- Allergy alert: This product contains natural rubber latex which may cause allergic reactions

Do not use

■Skin ulcers, breakage, and infections ■Pregnant women ■People with allergies

Stop use and ask a doctor if

excessive irritation of the skin develops

When using this product

avoid contact with the eyes

Keep out of reach of children.

If swallowed, get medical help or contact a Poison Control Center right away.

Directions

Clean the left and right upper arms，dry them,open the package，remove the backing paperand apply the cream on the outer side of the upper arms,wherethe fat accumulation is mostobvious and the sagging skin is the most obvious，every 4-8 hours，once a day, every 14days.cycle.

Inactive ingredients

Chinemys Reevesii Plastron, Chinese Softshell Shell, Chinese Cinnamon, Daemonorops Draco Fruit Resin, Dryobalanops Aromatica Resin, Duttaphrynus, Melanostictus Venom, Frankincense, Gum rosin, Laurocapram, Lycopodium Japonicum Top, Menthacamphor, Phryma Leptostachya Whole, Rubber